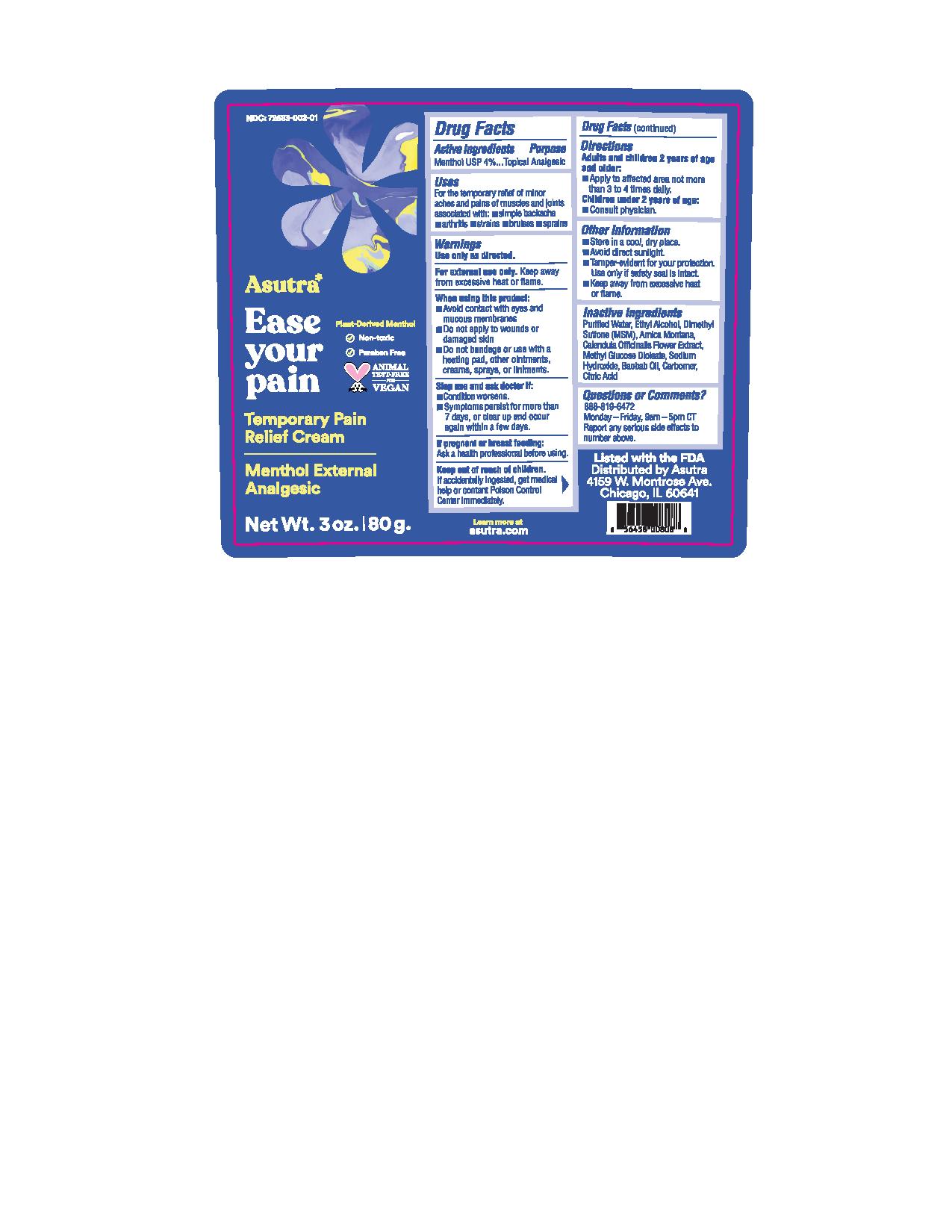 DRUG LABEL: Ease Your Pain
NDC: 72683-002 | Form: CREAM
Manufacturer: Proximity Capital Partners LLC dba Asutra
Category: otc | Type: HUMAN OTC DRUG LABEL
Date: 20241212

ACTIVE INGREDIENTS: MENTHOL 4 g/100 g
INACTIVE INGREDIENTS: ADANSONIA DIGITATA SEED OIL; ARNICA MONTANA; CALENDULA OFFICINALIS FLOWER; CARBOXYPOLYMETHYLENE; CITRIC ACID MONOHYDRATE; DIMETHYL SULFONE; ALCOHOL; METHYL GLUCOSE DIOLEATE; SODIUM HYDROXIDE; WATER

ACTIVE INGREDIENT

Menthol USP 4%

PURPOSE

Menthol USP 4% ........................... Topical Analgesic

INDICATIONS AND USAGE

For the temporary relief of minor aches and pains of muscles and joints associated with

- simple backache
- arthritis
- strains
- bruises
- sprains

WARNINGS

Use only as directed.

For external use only.Keep away from excessive heat or flame.

When using this product:

- Avoid contact with eyes and mucous membranes
- Do not apply to wounds or damaged skin
- Do not bandage or use with a heating pad, other ointments, creams, sprays, or liniments

Stop use and ask doctor if:

- Condition worsens
- Symptoms persist for more than 7 days, or clear up and occur again within a few days

PREGNANCY OR BREAST FEEDING

If pregnant or breastfeeding:Ask a health professional before using.

Keep out of reach of children. If accidentally ingested, get medical help or contact Poison Control Center immediately.

DOSAGE AND ADMINISTRATION

Adults and children 2 years of age and older:

- Apply to affected area not more than 3 to 4 times daily.

Children under 2 years of age:

- Consult physician.

STORAGE AND HANDLING

- Store in a cool, dry place.
- Avoid direct sunlight.
- Tamper-evident for your protection. Use only if safety seal is intact.
- Keep away from excessive heat or flame.

INACTIVE INGREDIENT

Purified Water, Ethyl Alcohol, Dimethyl Sulfone (MSM), Arnica Montana, Calendula Officinalis Flower Extract, Methyl Glucose Dioleate, Sodium Hydroxide, Baobab Oil, Carbomer, Citric Acid

QUESTIONS

888-819-6472

Monday - Friday, 9am - 5pm CT

Report any serious side effects to number above.